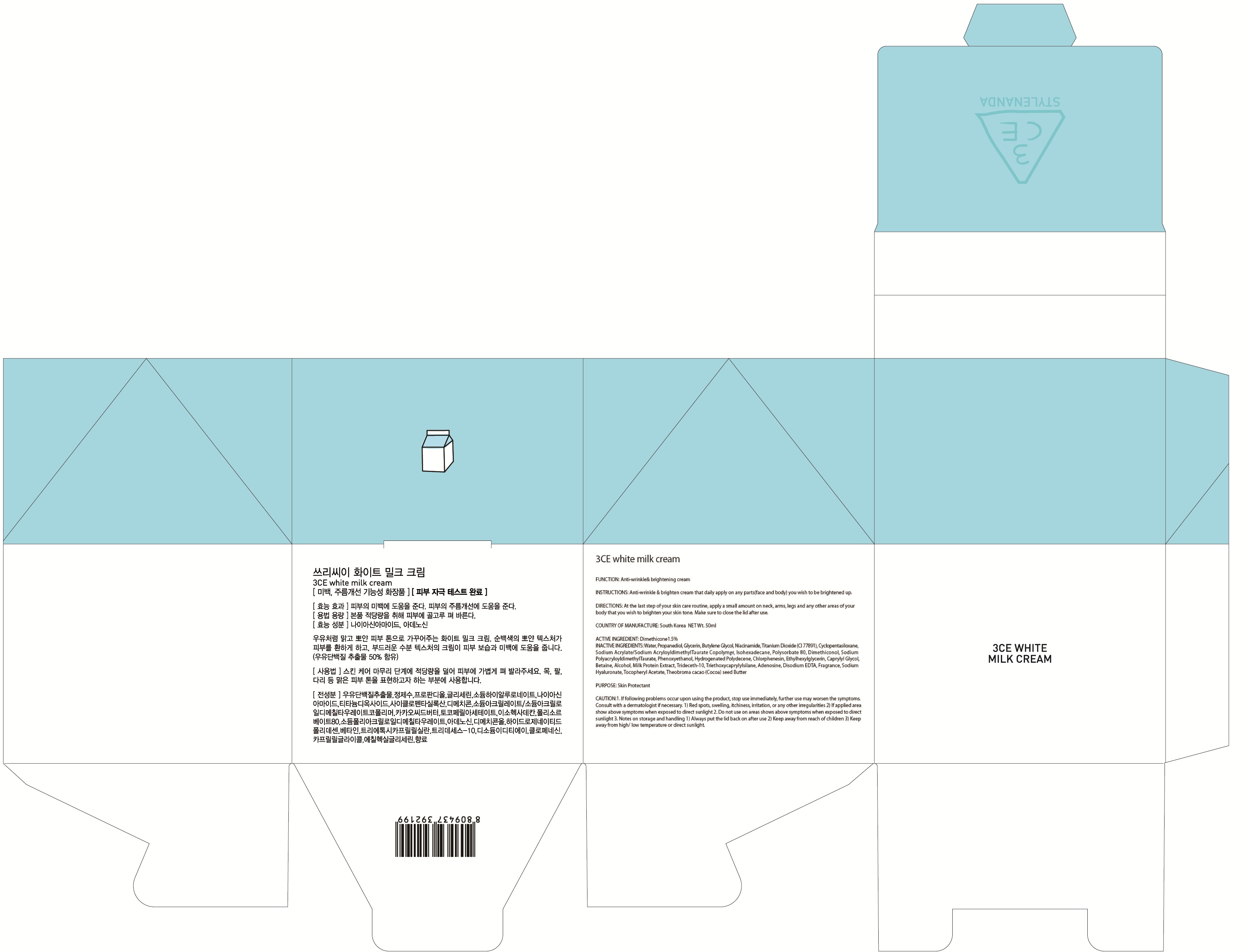 DRUG LABEL: 3CE WHITE MILK CREA M
NDC: 60764-125 | Form: CREAM
Manufacturer: Nanda Co., Ltd
Category: otc | Type: HUMAN OTC DRUG LABEL
Date: 20161014

ACTIVE INGREDIENTS: Dimethicone 0.75 g/50 mL
INACTIVE INGREDIENTS: Water; Propanediol

ACTIVE INGREDIENT

Active Ingredient: Dimethicone 1.5%

INACTIVE INGREDIENT

Inactive Ingredients: Water, Propanediol, Glycerin, Butylene Glycol, Niacinamide, Titanium Dioxide (CI 77891), Cyclopentasiloxane, Sodium Acrylate/Sodium AcryloyldimethylTaurate Copolymer, Isohexadecane, Polysorbate 80, Dimethiconol, Sodium PolyacryloyldimethylTaurate, Phenoxyethanol, Hydrogenated Polydecene, Chlorphenesin, Ethylhexylglycerin, Caprylyl Glycol, Betaine, Alcohol, Milk Protein Extract, Trideceth-10, Triethoxycaprylylsilane, Adenosine, Disodium EDTA, Fragrance, Sodium Hyaluronate, Tocopheryl Acetate, Theobroma cacao (Cocoa) seed Butter

PURPOSE

Purpose: Skin Protectant

CAUTION

CAUTION: 1. If following problems occur upon using the product, stop use immediately, further use may worsen the symptoms. Consult with a dermatologist if necessary. 1) Red spots, swelling, itchiness, irritation, or any other irregularities. 2) If applied area show above symptoms when exposed to direct sunlight. 2. Do not use on areas shows above symptoms when exposed to direct sunlight. 3. Notes on storage and handling 1) Always put the lid back on after use 2) Keep away from reach of children 3) Keep away from high/ low temperature or direct sunlight.

KEEP OUT OF REACH OF CHILDREN

Keep away from reach of children

INSTRUCTIONS

INSTRUCTIONS: Anti-wrinkle & brighten cream that daily apply on any parts(face and body) you wish to be brightened up.

Directions

Directions: At the last step of your skin care routine, apply a small amount on neck, arms, legs and any other areas of your body that you wish to brighten your skin tone. Make sure to close the lid after use.